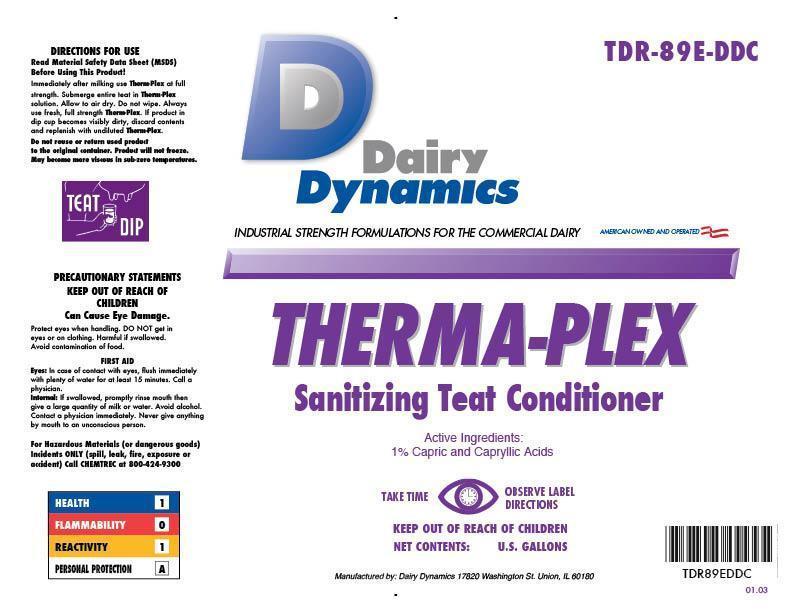 DRUG LABEL: Therma-Plex
NDC: 67351-989 | Form: SOLUTION
Manufacturer: Dairy Dynamics L.L.C.
Category: animal | Type: OTC ANIMAL DRUG LABEL
Date: 20150109

ACTIVE INGREDIENTS: CAPRYLIC/CAPRIC ACID 1.25 g/1 L
INACTIVE INGREDIENTS: WATER; PROPYLENE GLYCOL; PROPYLPARABEN; FD&C BLUE NO. 1; METHYL SALICYLATE; C9-11 PARETH-3; GLYCERIN; LANOLIN; ALOE VERA LEAF; POVIDONE K30

THERMA-PLEX
SANITIZING TEAT CONDITIONER

Dairy Dynamics

INDUSTRIAL STRENGTH FORMULATIONS FOR THE COMMERCIAL DAIRY

AMERICAN OWNED AND OPERATED

DIRECTIONS FOR USE

Read Material Safety Data Sheet (MSDS) Before Using This Product!

Immediately after milking use Therma-Plex at full strength. Submerge entire teat in Therma-Plex solution. Allow to air dry. Do not wipe. Always use fresh, full strength Therma-Plex. If product in dip cup becomes visibly dirty, discard contents and replenish with undiluted Therma-Plex.

PRECAUTIONS

Do not reuse or return used product to the original container. Product will not freeze. May become more viscous in sub-zero temperatures.

TEAT DIP

PRECAUTIONS

PRECAUTIONARY STATEMENTS

KEEP OUT OF REACH OF CHILDREN

Can Cause Eye Damage.

Protect eyes when handling. DO NOT get in eyes or on clothing. Harmful if swallowed. Avoid contamination of food.

FIRST AID

Eyes: in case of contact with eyes, flush immediately with plenty of water for at least 15 minutes. Call a physician.

Internal: if swallowed, promply rinse mouth then give a large quantity of milk or water. Avoid alcohol. Contact a physician immediately. Never give anything my mouth to an unconscious person.

For Hazardous Materials (or dangerous goods) Incidents ONLY (spill, leak, fire, exposure, or accident)

Call CHEMTREC at 800-424-9300

HEALTH 1

FLAMMABILITY 0

REACTIVITY 1

PERSONAL PROTECTION A

Active Ingredients: 1% Capric and Capryllic Acids

TAKE TIME OBSERVE LABEL DIRECTIONS

KEEP OUT OF REACH OF CHILDREN

NET CONTENTS: U.S. GALLONS

Manufactured by: Dairy Dynamics 17820 Washington St. Union, IL 60180

TDR-89E-DDC

TDR89EDDC